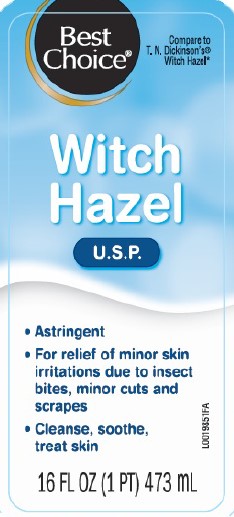 DRUG LABEL: Witch Hazel
NDC: 63941-822 | Form: LIQUID
Manufacturer: Valu Merchandisers Company
Category: otc | Type: HUMAN OTC DRUG LABEL
Date: 20260216

ACTIVE INGREDIENTS: WITCH HAZEL 860 mg/1 mL
INACTIVE INGREDIENTS: ALCOHOL

Best Choice 822.001/822AA
Witch Hazel USP

Active Ingredient

Witch hazel 86%

Purpose

Astringent

Use

for relief of minor skin irritations due to:
•insect bites • minor cuts •minor scrapes

Warnings

For external use only

When using this product

- avoid contact with the eyes. If contact occurs, rinse thoroughly with water.

Stop use and ask a doctor if

- condition worsens or symptoms persists for more than 7 days

Keep out of reach of children.

If swallowed, get medical help or contact a Poison Control Center right away.

Directions

apply as often as needed

Inactive ingredient

alcohol 14% by volume

adverse reactons

*This productis not manufactured or distributed by Dickinson Brands, Inc., distributor of T. N. Dickinson's ®Witch Hazel.

PROUDLY DISTRIBUTED BY: VALUE MERCHANDISERS, CO.

5000 KANSAS AVE, KANSAS CITY, KS 66106

Scan here for more information.

Call 1-844-292-1112 for more information.

BEST CHOICE

70038-1021-VIJON

Pat. D675, 101

Principal Panel Display

Best Choice ®

Compare to T.N. Dickinson's ®Witch Hazel*

Witch

Hazel

U.S.P.

- Astringent
- For relief of minor skin irritations due to insect bites, minor cuts and scrapes
- Cleanses, soothe, treat skin

16 FL OZ (1 PT) 473 mL